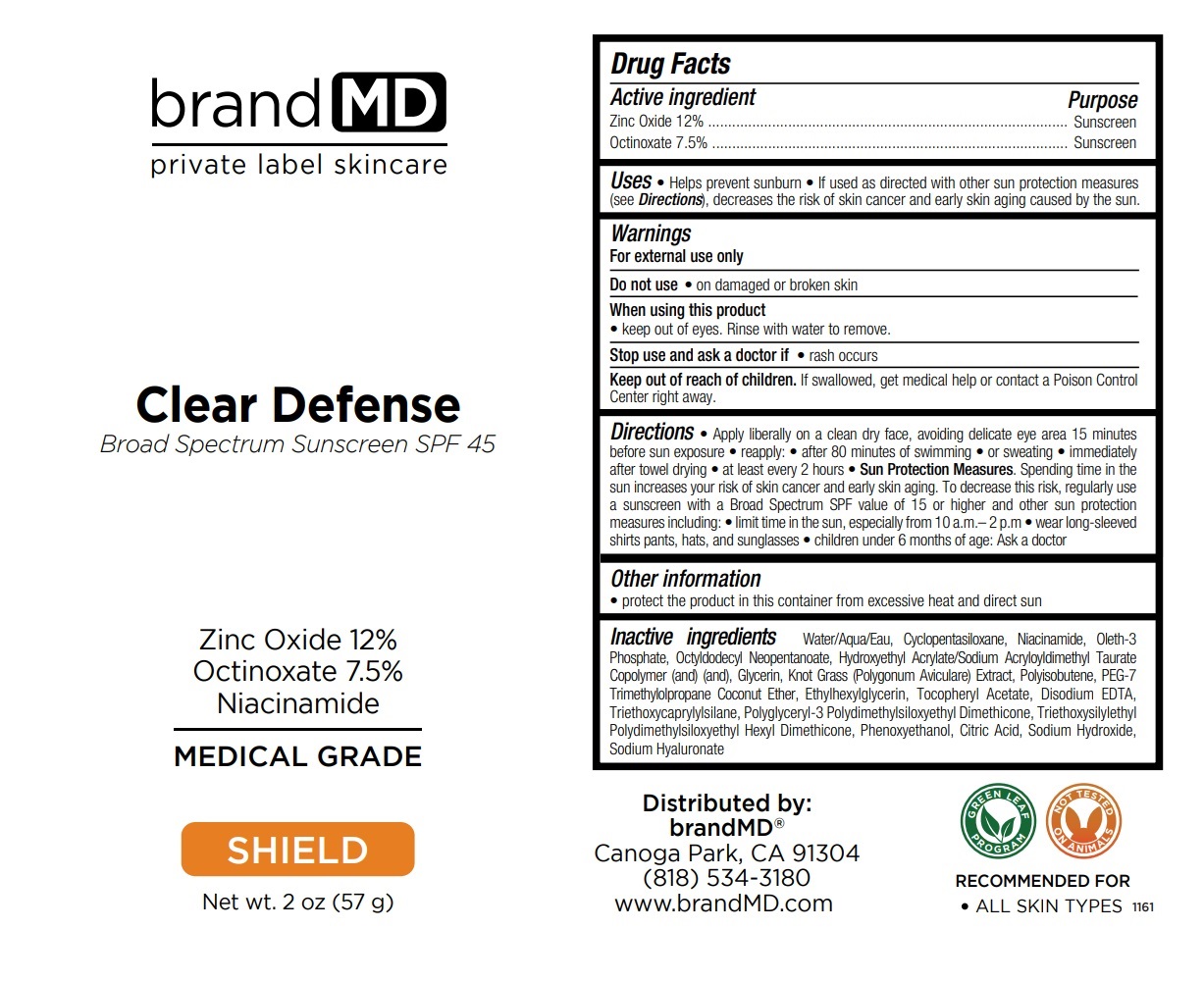 DRUG LABEL: Clear Defense SPF 45
NDC: 72957-003 | Form: CREAM
Manufacturer: Private Label Skin Care
Category: otc | Type: HUMAN OTC DRUG LABEL
Date: 20250227

ACTIVE INGREDIENTS: ZINC OXIDE 12 g/100 g; OCTINOXATE 7.5 g/100 g
INACTIVE INGREDIENTS: WATER; CYCLOMETHICONE 5; NIACINAMIDE; OLETH-3 PHOSPHATE; OCTYLDODECYL NEOPENTANOATE; HYDROXYETHYL ACRYLATE/SODIUM ACRYLOYLDIMETHYL TAURATE COPOLYMER (100000 MPA.S AT 1.5%); GLYCERIN; POLYGONUM AVICULARE TOP; POLYISOBUTYLENE (1000 MW); PEG-7 TRIMETHYLOLPROPANE COCONUT ETHER; ETHYLHEXYLGLYCERIN; .ALPHA.-TOCOPHEROL ACETATE, DL-; EDETATE DISODIUM ANHYDROUS; TRIETHOXYCAPRYLYLSILANE; POLYGLYCERYL-3 POLYDIMETHYLSILOXYETHYL DIMETHICONE (4000 MPA.S); TRIETHOXYSILYLETHYL POLYDIMETHYLSILOXYETHYL HEXYL DIMETHICONE; PHENOXYETHANOL; CITRIC ACID MONOHYDRATE; SODIUM HYDROXIDE; HYALURONATE SODIUM

Clear Defense SPF 45

Active ingredient

Zinc Oxide 12%

Octinoxate 7.5%

Purpose

Sunscreen

Uses

• Helps prevent sunburn • If used as directed with other sun protection measures (see Directions), decreases the risk of skin cancer and early skin aging caused by the sun.

Warnings

For external use only

Do not use • on damaged or broken skin

When using this product
• keep out of eyes. Rinse with water to remove.

Stop use and ask a doctor if • rash occurs

Keep out of reach of children. If swallowed, get medical help or contact a Poison Control Center right away.

Directions

• Apply liberally on a clean dry face, avoiding delicate eye area 15 minutes before sun exposure • reapply: • after 80 minutes of swimming • or sweating • immediately after towel drying • at least every 2 hours • Sun Protection Measures. Spending time in the sun increases your risk of skin cancer and early skin aging. To decrease this risk, regularly use a sunscreen with a Broad Spectrum SPF value of 15 or higher and other sun protection measures including: • limit time in the sun, especially from 10 a.m.– 2 p.m • wear long-sleeved shirts pants, hats, and sunglasses • children under 6 months of age: Ask a doctor

Other information

• protect the product in this container from excessive heat and direct sun

Inactive ingredients

Water/Aqua/Eau, Cyclopentasiloxane, Niacinamide, Oleth-3 Phosphate, Octyldodecyl Neopentanoate, Hydroxyethyl Acrylate/Sodium Acryloyldimethyl Taurate Copolymer (and), Glycerin, Knot Grass (Polygonum Aviculare) Extract, Polyisobutene, PEG-7 Trimethylolpropane Coconut Ether, Ethylhexylglycerin, Tocopheryl Acetate, Disodium EDTA, Triethoxycaprylylsilane, Polyglyceryl-3 Polydimethylsiloxyethyl Dimethicone, Triethoxysilylethyl Polydimethylsiloxyethyl Hexyl Dimethicone, Phenoxyethanol, Citric Acid, Sodium Hydroxide, Sodium Hyaluronate

brand MD

Broad Spectrum Sunscreen

Zinc Oxide 12%
Octinoxate 7.5%
Niacinamide

MEDICAL GRADE

SHIELD

RECOMMENDED FOR
• ALL SKIN TYPES

GREEN LEAF PROGRAM

NOT TESTED ON ANIMALS

Distributed by:
brandMD®
Canoga Park, CA 91304
(818) 534-3180
www.brandMD.com